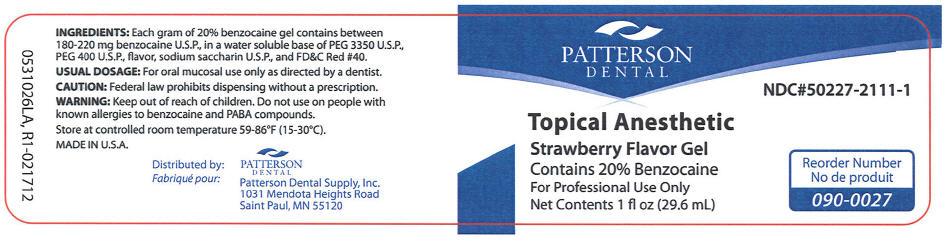 DRUG LABEL: Topical Anesthetic 
NDC: 50227-2111 | Form: GEL
Manufacturer: Patterson Dental Supply Inc
Category: otc | Type: HUMAN OTC DRUG LABEL
Date: 20120409

ACTIVE INGREDIENTS: Benzocaine 220 mg/1 g
INACTIVE INGREDIENTS: Polyethylene Glycol 400; Saccharin Sodium Dihydrate; Polyethylene Glycol 3350; Water

Patterson Topical Anesthetic Strawberry Flavor

ACTIVE INGREDIENT

INGREDIENTS

Each gram of 20% benzocaine gel contains between 180-220 mg benzocaine U.S.P., in a water soluble base of PEG 3350 U.S.P., PEG 400 U.S.P., flavor, sodium saccharin U.S.P., and FD&C Red #40.

USUAL DOSAGE

For oral mucosal use only as directed by a dentist.

INDICATIONS AND USAGE

CAUTION

Federal law prohibits dispensing without a prescription.

WARNING

Keep out of reach of children.

Do not use on people with known allergies to benzocaine and PABA compounds.

HOW SUPPLIED

STORAGE AND HANDLING

Store at controlled room temperature 59-86°F (15-30°C).

MADE IN U.S.A.
Distributed by:
PATTERSON DENTAL
Patterson Dental Supply, Inc.
1031 Mendota Heights Road
Saint Paul, MN 55120

PRINCIPAL DISPLAY PANEL - 29.6 mL Jar Label

PATTERSON
DENTAL

NDC#50227-2111-1

Topical Anesthetic

Strawberry Flavor Gel

Contains 20% Benzocaine

For Professional Use Only

Net Contents 1 fl oz (29.6 mL)

Reorder Number
090-0027